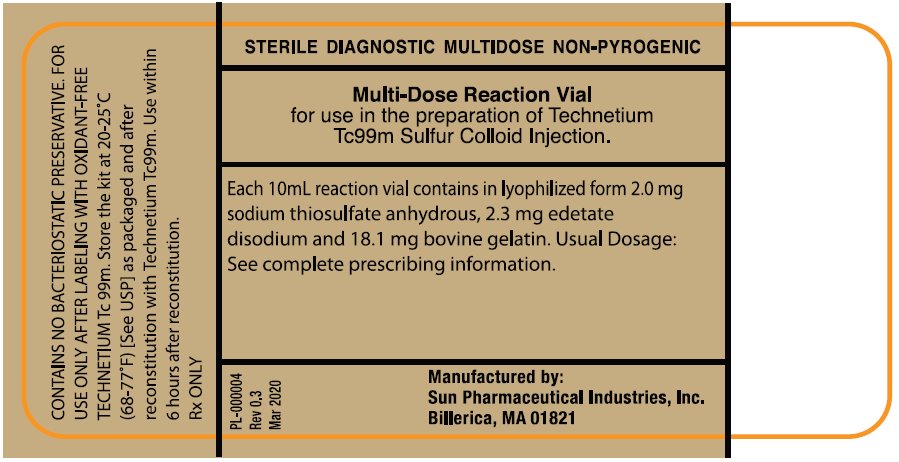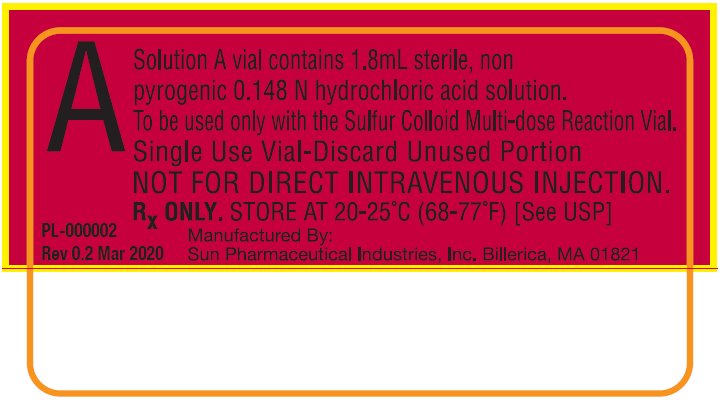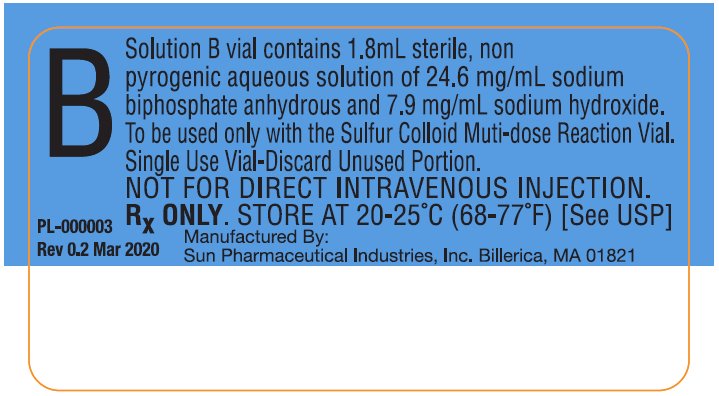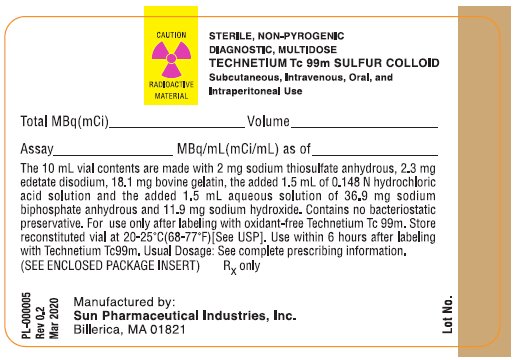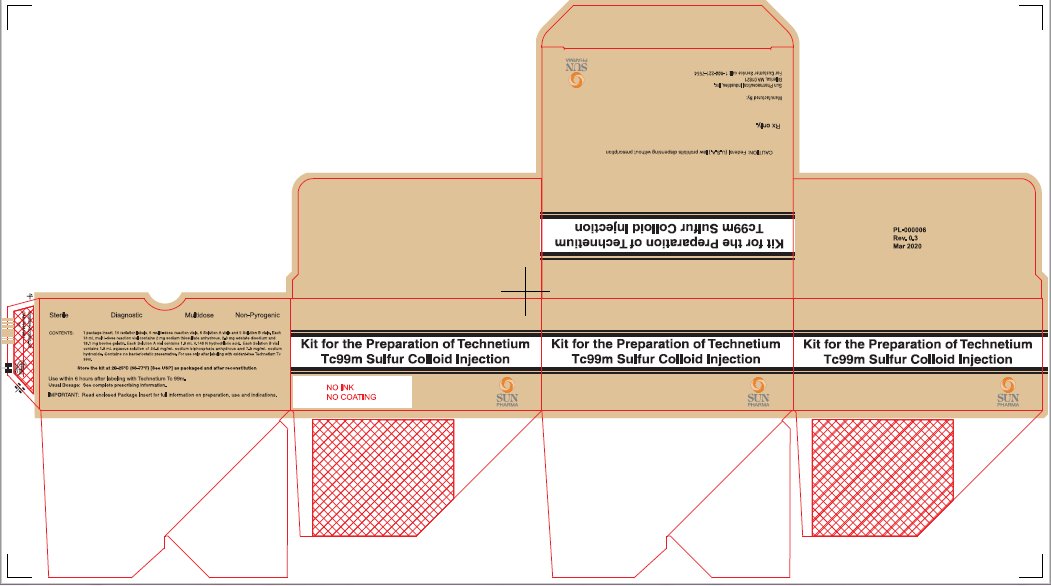 DRUG LABEL: Kit for the Prepartion of Technetium Tc99m Sulfur Colloid
NDC: 45567-0030 | Form: KIT | Route: INTRAVENOUS
Manufacturer: Sun Pharmaceutical Industries, Inc.
Category: prescription | Type: HUMAN PRESCRIPTION DRUG LABEL
Date: 20240913

ACTIVE INGREDIENTS: TECHNETIUM TC-99M SULFUR COLLOID 10 mCi/10 mL
INACTIVE INGREDIENTS: SODIUM THIOSULFATE ANHYDROUS 2 mg/10 mL; EDETATE DISODIUM 2.3 mg/10 mL; GELATIN, UNSPECIFIED 18.1 mg/10 mL; HYDROCHLORIC ACID 0.148 mol/3 mL; SODIUM HYDROXIDE 7.9 mg/3 mL; SODIUM PHOSPHATE, MONOBASIC, ANHYDROUS 24.6 mg/3 mL

HIGHLIGHTS OF PRESCRIBING INFORMATION

These highlights do not include all the information needed to use Kit for the Preparation of Technetium Tc 99m Sulfur Colloid Injection.
See full prescribing information for Kit for the Preparation of Technetium Tc 99m Sulfur Colloid Injection.
Kit for the Preparation of Technetium Tc 99m Sulfur Colloid Injection for Subcutaneous, Intraperitoneal, Intravenous and Oral Use.
Initial U.S. Approval: 1978

1 INDICATIONS AND USAGE

Technetium Tc 99m Sulfur Colloid Injection is a radioactive diagnostic agent indicated (1):

In adults, to assist in the:

- localization of lymph nodes draining a primary tumor in patients with breast cancer or malignant melanoma when used with a hand-held gamma counter.
- evaluation of peritoneo-venous (LeVeen) shunt patency in adults.

In adults and pediatric patients, for:

- imaging areas of functioning reticuloendothelial cells in the liver, spleen and bone marrow.
- studies of esophageal transit and gastroesophageal reflux, and detection of pulmonary aspiration of gastric contents.

2 DOSAGE AND ADMINISTRATION

Minimize Tc99m Sulfur Colloid radiation exposure and measure patient doses immediately before administration.

- Breast cancer or malignant melanoma setting: by subcutaneous injection, 3.7 to 37 MBq (0.1 to 1 mCi in volumes ranging from 0.1 to 1 mL) (2.1).
- Peritoneo-venous (LeVeen) shunt setting in adults: (2.1)
  - by intraperitoneal injection: 37 to 111 MBq (1 to 3 mCi);
  - by percutaneous transtubal injection: 12 to 37 MBq (0.3 to 1 mCi) in a volume not to exceed 0.5 mL.
- Imaging areas of functioning reticuloendothelial cells by intravenous injection (2.1):
- In adults:
- Liver/spleen imaging: 37 to 296 MBq (1 to 8 mCi);
- Bone marrow imaging: 111 to 444 MBq (3 to 12 mCi);
- In pediatric patients:
- Liver/spleen imaging in newborns: 7.4 to 18.5 MBq (0.2 to 0.5 mCi);
- Liver/spleen imaging in children: 0.56 to 2.78 MBq (0.015 to 0.075 mCi) per kg of body weight (BW);
- Bone marrow imaging: 1.11 to 5.55 MBq (0.03 to 0.15 mCi) per kg of BW.
- Gastroesophageal and pulmonary aspiration studies by oral route (2.1):
- In adults:
- Gastroesophageal studies: 5.55 to 11.1 MBq (0.15 to 0.30 mCi);
- Pulmonary aspiration studies: 11.1 to 18.5 MBq (0.30 to 0.50 mCi).
- In pediatric patients:
- 3.7 to 11.1 MBq (0.10 to 0.30 mCi).

3 DOSAGE FORMS AND STRENGTHS

The Kit for the Preparation of Technetium Tc 99m Sulfur Colloid Injection is supplied as a package that contains 5 kits. Each kit contains three vials: one 10 mL multi-dose Reaction Vial, a Solution A vial and a Solution B vial. The vials contain the sterile non-pyrogenic, non-radioactive ingredients necessary to produce Technetium Tc 99m Sulfur Colloid Injection (3).

4 CONTRAINDICATIONS

None

5 WARNINGS AND PRECAUTIONS

Anaphylactic reactions including rare fatalities have occurred following intravenously administered Technetium Tc 99m Sulfur Colloid. Have resuscitation equipment and personnel immediately available (5.1).

6 ADVERSE REACTIONS

The most frequently reported adverse reactions include rash, urticaria, anaphylactic shock, and hypotension. (6)

To report SUSPECTED ADVERSE REACTIONS, contact Sun Pharmaceutical Industries, Inc. at 1-800-221-7554 or FDA at 1-800-FDA-1088 or www.fda.gov/medwatch

8 USE IN SPECIFIC POPULATIONS

Lactation: Advise a lactating woman to pump and discard breast milk for 24 hours and minimize close contact with infants for 6 hours after receiving a Technetium Tc 99m Sulfur Colloid Injection (8.2).

FULL PRESCRIBING INFORMATION

1 INDICATIONS AND USAGE

Technetium Tc 99m Sulfur Colloid Injection is indicated:

In adults, to assist in the:

- localization of lymph nodes draining a primary tumor in patients with breast cancer or malignant melanoma when used with a hand-held gamma counter.
- evaluation of peritoneo-venous (LeVeen) shunt patency.

In adults and pediatric patients, for imaging:

- areas of functioning reticuloendothelial cells in the liver, spleen and bone marrow.
- studies of esophageal transit and, gastroesophageal reflux, and detection of pulmonary aspiration of gastric contents.

2 DOSAGE AND ADMINISTRATION

Technetium Tc 99m Sulfur Colloid Injection emits radiation. Use procedures to minimize radiation exposure. Measure patient dose by a suitable radioactivity calibration system immediately before administration.

2.1 Recommended Doses

- Breast cancer or malignant melanoma setting in adults: 3.7 to 37 MBq (0.1 to 1 mCi) in volumes ranging from 0.1 to 1 mL by subcutaneous injection.
- Peritoneo-venous (LeVeen) shunt setting in adults: 37 to 111 MBq (1 to 3 mCi) by intraperitoneal injection, or 12 to 37 MBq (0.3 to 1 mCi) in a volume not to exceed 0.5 mL by percutaneous transtubal (efferent limb) injection. Patient repositioning or other measures may be used to help assure uniform mixing of the radiopharmaceutical with peritoneal fluid.
- Imaging areas of functioning reticuloendothelial cells:
- In adults:
  1. liver/spleen imaging: 37 to 296 MBq (1 to 8 mCi) by intravenous injection;
  2. bone marrow imaging: 111 to 444 MBq (3 to 12 mCi) by intravenous injection.
- In pediatric patients:
  1. liver/spleen imaging in children: 0.56 to 2.78 MBq (0.015 to 0.075 mCi) per kg of body weight (BW) by intravenous injection;
  2. liver/spleen imaging in newborns: 7.4 to 18.5 MBq (0.20 to 0.50 mCi) by intravenous injection;
  3. bone marrow imaging: 1.11 to 5.55 MBq (0.03 to 0.15 mCi) per kg of BW by intravenous injection.
- Gastroesophageal and pulmonary aspiration imaging studies:
- In adults:
  1. gastroesophageal studies: 5.55 to 11.1 MBq (0.15 to 0.30 mCi) by oral administration;
  2. pulmonary aspiration studies: 11.1 to 18.5 MBq (0.30 to 0.50 mCi) by oral administration.
- In pediatric patients:
  1. gastroesophageal and pulmonary aspiration studies: 3.7 to 11.1 MBq (0.10 to 0.30 mCi) by oral or nasogastric tube administration. For oral administration, combine the radiopharmaceutical with a milk feeding. For nasogastric tube administration, administer the radiopharmaceutical into the stomach then instill a normal volume of dextrose or milk feeding.

2.2 Drug Preparation and Administration

- The contents of the two Solution vials, the Solution A vial containing the appropriate acidic solution and the Solution B vial containing the appropriate buffer solution, are intended only for use in the preparation of the Technetium Tc 99m Sulfur Colloid Injection and are not to be directly administered to the patient.
- Do not use Sodium Pertechnetate Tc 99m containing oxidants to reconstitute this kit.
- The contents of the kit are not radioactive. However, after the Sodium Pertechnetate Tc 99m is added, maintain adequate shielding of the final preparation. Wear waterproof gloves during the preparation procedure.
- Do not use Sodium Pertechnetate Tc 99m containing more than 10 micrograms per mL of aluminum ion because a flocculent precipitate may occur and such a precipitate may localize in the lung.
- The contents of the kit are sterile and non-pyrogenic. This preparation contains no bacteriostatic preservative. Follow the directions carefully and adhere strictly to aseptic procedures during preparation.

Prepare Technetium Tc 99m Sulfur Colloid Injection by the following aseptic procedure:

1. Remove the dark brown plastic cap from the Sulfur Colloid multi-dose Reaction Vial and swab the top of the vial closure with alcohol to sterilize the surface. Complete the radiation label and affix to the vial. Place the vial in an appropriate lead-capped radiation shield labeled and identified.
2. With a sterile shielded syringe, aseptically obtain 1 to 3 mL of a suitable, oxidant-free sterile and non-pyrogenic Sodium Pertechnetate Tc 99m, each milliliter containing a maximum activity of 18,500 MBq (500 mCi).
3. Aseptically add the Sodium Pertechnetate Tc 99m to the vial.
4. Place a lead cover on the vial shield and dissolve the reagent by gentle swirling.
5. Just before use, remove the red cap from the Solution A vial and swab the top of the vial closure with alcohol to sterilize the surface. Using a sterile needle and syringe, aseptically withdraw 1.5 mL Solution A from the vial. Aseptically Inject 1.5mL Solution A into the multi-dose Reaction Vial and swirl again.
6. Transfer the multi-dose Reaction Vial from vial shield and place in a vigorously boiling water bath (water bath should be shielded with 1/8” to 1/4” lead) deep enough to cover the entire liquid contents of the vial. Keep the vial in the water bath for five minutes.
7. Remove the multi-dose Reaction Vial from the water bath and place in the lead shield and allow to cool for three minutes. Swab the vial closure again with an antiseptic.
8. Just before use, remove the blue cap from the Solution B vial and swab the top of the vial closure with alcohol to sterilize the surface. Using a sterile needle and syringe, aseptically withdraw 1.5 mL Solution B from the vial. Aseptically Inject 1.5 mL Solution B into the multi-dose Reaction Vial and swirl again.
9. Record time and date of preparation.
10. Allow the preparation to cool to body temperature before use. Maintain adequate shielding of the radioactive colloid preparation at all times.
11. Where appropriate, dilute the preparation with sterile Sodium Chloride Injection to bring the dosage to within the recommended range.
12. Mix the multi-dose Reaction Vial and aseptically withdraw material with a sterile shielded syringe for use within 6 hours of preparation. For optimum results this time should be minimized. The vial contains no bacteriostatic preservative. Store the reconstituted vial at 20 to 25°C (68 to77°F). Discard vial 6 hours after reconstitution.
13. Carefully agitate the shielded syringe immediately prior to administration of sulfur colloid to avoid particles aggregation and non-uniform distribution of radioactivity.

Measure the patient dose by a suitable radioactivity calibration system immediately before administration. Check radiochemical purity before patient administration.

Inspect Technetium Tc 99m Sulfur Colloid Injection visually for particulate matter and discoloration before administration, whenever solution and container permit. Do not administer the drug if it contains particulate matter or discoloration; dispose of these unacceptable or unused preparations in a safe manner, in compliance with applicable regulations.

2.3 Radiation Dosimetry

- Subcutaneous injection to assist in lymph node localization

Table 1. Estimated Adult Absorbed Radiation Doses from Subcutaneous Administration of Technetium Tc 99m Sulfur Colloid Injection (mSv/MBq and rem/mCi)^1
Target Organ | mSv/MBq | rem/mCi
Injection Site | 9.51 | 35. 2
Lymph Nodes | 0.951 | 3.52
Liver | 0.0028 | 0.0104
Spleen | 0.0017 | 0.00629
Bone Marrow | 0.0019 | 0.00703
Testes | 0.0009 | 0.0033
Ovaries | 0.00018 | 0.00066
Total Body | 0.004 | 0.0148

^1Bergqvist L, Strand S-E, Persson B, et al. Dosimetry in
Lymphoscintigraphy of Tc 99m Antimony Sulfide Colloid,
J Nucl Med, 23: 698-705, 1982.

- Intravenous Injection

Adult Radiation Doses

Table 2. Estimated Adult Absorbed Radiation Doses from Technetium Tc 99m Sulfur Colloid Injection Administration (mSv/MBq and rem/mCi)^2
 |  |  | Diffuse Parenchymal Disease
Target Organ | Normal Liver |  | Early to Intermediate |  | Intermediate to Advanced
Target Organ | mSv/MBq | rem/mCi | mSv/MBq | rem/mCi | mSv/MBq | rem/mCi
Liver | 0.091 | 0.338 | 0.058 | 0.213 | 0.044 | 0.163
Spleen | 0.058 | 0.213 | 0.074 | 0.275 | 0.115 | 0.425
Bone Marrow | 0.008 | 0.028 | 0.012 | 0.045 | 0.021 | 0.079
Testes | 0.0003 | 0.001 | 0.0005 | 0.002 | 0.0008 | 0.003
Ovaries | 0.0016 | 0.006 | 0.0022 | 0.008 | 0.0032 | 0.012
Total Body | 0.005 | 0.019 | 0.005 | 0.019 | 0.005 | 0.018

^2Modified from Summary of Current Radiation Dose Estimates to Humans with Various Liver Conditions from 99m Tc-Sulfur Colloid, MIRD Dose Estimate Report No 3, J Nucl Med 16: 108A - 108B, 197

Pediatric Radiation Doses

Table 3A. Estimated Pediatric Absorbed Radiation Doses from Technetium Tc 99m Sulfur Colloid Injection Administration of 1 MBq and 1 mCi for Liver/Spleen and Bone Marrow Imaging (in mSv/MBq and rem/mCi)^3
Age; Body Weight |  | Newborn; 3.5 kg | 1 year; 12.1 kg | 5 years; 20.3 kg | 10 years; 33.5 kg | 15 years; 55 kg
Absorbed Dose
Target Organ
Liver | mSv/MBq | 0.86 | 0.38 | 0.22 | 0.18 | 0.13
Liver | rem/mCi | 3.2 | 1.4 | 0.82 | 0.67 | 0.49
Spleen | mSv/MBq | 0.76 | 0.32 | 0.18 | 0.13 | 0.09
Spleen | rem/mCi | 2.8 | 1.2 | 0.65 | 0.49 | 0.33
Red Marrow | mSv/MBq | 0.16 | 0.05 | 0.03 | 0.022 | 0.01
Red Marrow | rem/mCi | 0.58 | 0.18 | 0.11 | 0.081 | 0.036
Ovaries | mSv/MBq | 0.04 | 0.02 | 0.0103 | 0.0043 | 0.0022
Ovaries | rem/mCi | 0.14 | 0.064 | 0.038 | 0.016 | 0.008
Testes | mSv/MBq | 0.011 | 0.006 | 0.004 | 0.004 | 0.001
Testes | rem/mCi | 0.04 | 0.021 | 0.013 | 0.014 | 0.002
Total Body | mSv/MBq | 0.032 | 0.026 | 0.018 | 0.012 | 0.006
Total Body | rem/mCi | 0.12 | 0.096 | 0.066 | 0.043 | 0.022

^3from Age-dependent “S” values of Henrichs et al, Berlin 1982, except for the 1-year old.
The 1-year old “S” values were taken from phantom work of the Metabolism and Dosimetry Group at ORNL

Table 3B. Estimated Pediatric Maximum Absorbed Radiation Doses from Administration of the Maximum Recommended Dose for Technetium Tc 99m Sulfur Colloid Injection (mSv and rem)^3
Age; Body Weight |  | Newborn; 3.5 kg |  | 1 year; 12.1 kg |  | 5 years; 20.3 kg |  | 10 years; 33.5 kg |  | 15 years; 55 kg
Maximum Recommended Dose: |  | a* | b* | a* | b* | a* | b* | a* | b* | a* | b*
MBq |  | 18.5 | 22.2 | 33.3 | 67.3 | 55.5 | 114.7 | 92.5 | 186.1 | 151.7 | 307.1
mCi |  | 0.5 | 0.6 | 0.9 | 1.82 | 1.5 | 3.1 | 2.5 | 5.03 | 4.1 | 8.3
Maximum Absorbed Dose from Maximum Recommended Dose Administered (mSv and rem)
Target Organ
Liver | mSv | 16 | 19.2 | 12.6 | 25.46 | 12.3 | 25.42 | 16.7 | 33.6 | 20.1 | 40.69
Liver | rem | 1.6 | 1.92 | 1.26 | 2.55 | 1.23 | 2.54 | 1.67 | 3.36 | 2.01 | 4.07
Spleen | mSv | 14 | 16.8 | 10.8 | 21.83 | 9.75 | 20.15 | 12.2 | 24.55 | 13.5 | 27.33
Spleen | rem | 1.4 | 1.68 | 1.08 | 2.18 | 0.98 | 2.02 | 1.22 | 2.45 | 1.35 | 2.73
Red Marrow | mSv | 2.9 | 3.48 | 1.62 | 3.27 | 1.65 | 3.41 | 2.03 | 4.08 | 1.48 | 3
Red Marrow | rem | 0.29 | 0.35 | 0.16 | 0.33 | 0.17 | 0.34 | 0.2 | 0.41 | 0.15 | 0.3
Ovaries | mSv | 0.7 | 0.84 | 0.58 | 1.17 | 0.57 | 1.18 | 0.4 | 0.8 | 0.34 | 0.69
Ovaries | rem | 0.07 | 0.084 | 0.058 | 0.117 | 0.057 | 0.118 | 0.04 | 0.08 | 0.034 | 0.069
Testes | mSv | 0.2 | 0.24 | 0.19 | 0.38 | 0.2 | 0.41 | 0.35 | 0.7 | 0.09 | 0.18
Testes | rem | 0.02 | 0.024 | 0.019 | 0.038 | 0.02 | 0.041 | 0.035 | 0.07 | 0.009 | 0.018
Total Body | mSv | 0.6 | 0.72 | 0.86 | 1.74 | 0.99 | 2.05 | 1.07 | 2.15 | 0.9 | 1.82
Total Body | rem | 0.06 | 0.072 | 0.086 | 0.174 | 0.099 | 0.205 | 0.107 | 0.215 | 0.09 | 0.182

*aliver/spleen imaging

*bbone marrow imaging

^3from Age-dependent “S” values of Henrichs et al., Berlin 1982, except for the 1-year old.
The 1-year old “S” values were taken from phantom work of the Metabolism and Dosimetry Group at ORNL

- Oral Administration

Table 4. Adult Radiation Absorbed Dose from Oral Administration of 1mCi of Technetium Tc99m Sulfur Colloid Injection (mSv/MBq and rem/mCi)
Target Organ | Assumed Residence Time (hr.) | mSv/MBq | rem/mCi
Stomach Wall | 1.5 | 0.038 | 0.14
Small Intestine | 4 | 0.07 | 0.26
Upper Large Intestine Wall | 13 | 0.13 | 0.48
Upper Large Intestine Wall | 24 | 0.089 | 0.33
Ovaries | - | 0.026 | 0.096
Testes | - | 0.001 | 0.005
Total Body | - | 0.005 | 0.018

- Intraperitoneal Injection

Table 5. Adult Absorbed Radiation Dose from Intraperitoneal Injection of 3 mCi of Technetium Tc 99m Sulfur Colloid (mSv/MBq and rem/mCi)
Target Organ | Shunt Open |  | Shunt Closed
Target Organ | mSv/MBq | rem/mCi | mSv/MBq | rem/mCi
Liver | 0.092 | 0.34 | 0.015 | 0.056
Ovaries and Testes | 0.0003 to 0.0016 | 0.0012 to 0.006 | 0.015 | 0.056
Organs in the Peritoneal Cavity | - | - | 0.015 | 0.056
Total Body | 0.0049 | 0.0180 | 0.005 | 0.019

Assumptions: Calculations for the absorbed radiation dose are based upon an effective half-time of 3 hours for the open shunt and 6.02 hours for the closed shunt and an even distribution of the radiopharmaceutical in the peritoneal cavity with no biological clearance.

- Other Exposure Estimates

Table 6. Radiation Doses to Hospital Personnel (µSv/MBq and mrem/mCi)
Technician | Preparation of Drug* |  | Administered Drug
Target | µSv/MBq | mrem/mCi | µSv/MBq | mrem/mCi
Extremity Dose | 0.016 | 0.0575 | 0.07 | 0.25
Whole Body Dose | 0.0007 | 0.0025 | 0.003 | 0.0125

*Using shielded vial and syringe

2.4 Imaging Considerations

Breast cancer or malignant melanoma setting in adults:

- In clinical studies, patients received injection of Technetium Tc 99m Sulfur Colloid Injection and a concomitant blue dye tracer in order to enhance the ability to detect lymph nodes. Visual inspection was performed to identify the blue-labeled nodes and a hand held gamma counter was used to identify nodes concentrating the radiopharmaceutical. Multiple methods were used to detect the concentrated radioactivity within lymph nodes. For example, investigators used thresholds of background radioactivity to localize nodes containing a minimum of radioactive counts 3 times higher than the background or containing at least 10 fold higher counts than contiguous nodes .
- In clinical studies of patients with malignant melanoma, preoperative lymphoscintigraphy was usually performed using planar imaging techniques to establish a road map of nodal basins and to facilitate intraoperative identification of lymph nodes. [see Clinical Studies (14)]
- Technetium Tc 99m Sulfur Colloid Injection and other tracers may not localize all lymph nodes and the tracers may differ in their extent of lymph node localization. The lymph node localization of Technetium Tc 99m Sulfur Colloid Injection is dependent upon the underlying patency and structure of the lymphatic system, the extent of functional reticuloendothelial cells within lymph nodes and the radiopharmaceutical injection technique. Distortion of the underlying lymphatic system architecture and function by prior surgery, radiation or extensive metastatic disease may result in failure of the radiopharmaceutical and other tracers to localize lymph nodes. The use of Technetium Tc 99m Sulfur Colloid Injection is intended to supplement palpation, visual inspection and other procedures important to lymph node localization. [see Clinical Studies (14)].
- Peritoneo-venous (LeVeen) shunt setting in adults: Following administration of Technetium Tc 99m Sulfur Colloid Injection into the peritoneal cavity, the radiopharmaceutical mixes with the peritoneal fluid. Clearance from the peritoneal cavity varies from insignificant, which may occur with complete shunt blockage, to very rapid clearance with subsequent transfer into the systemic circulation when the shunt is patent. Following transfer into the systemic circulation, the radiopharmaceutical concentrates within the liver (a target organ). Obtain serial images of both the shunt and liver. An adequate evaluation of the difference between total blockage of the shunt and partial blockage may not be feasible in all cases. Transperitoneal absorption of sulfur colloid into the systemic circulation may occur, but it occurs slowly. Therefore, the most definitive scintigraphic evaluation of shunt patency will generally be obtained if there is visualization of both the shunt itself and the liver and/or spleen within the first three hours post intraperitoneal injection of the radiopharmaceutical.
- Imaging areas of functioning reticuloendothelial cells in liver, spleen or bone marrow: Altered biodistribution with lung and soft tissue uptake instead of reticuloendothelial system has been reported after intravenous injection. The size and physical-chemical properties of the sulfur colloid particles formed from the components of the kit may determine the biodistribution of the colloid and its uptake by the reticuloendothelial system. Diseases affecting the reticuloendothelial system may also alter the expected uptake pattern.
- Gastroesophageal and pulmonary aspiration imaging studies: To facilitate the imaging of gastroesophageal reflux consider administering Sulfur Colloid by nasogastric tube.

3 DOSAGE FORMS AND STRENGTHS

Kit for the Preparation of Technetium Tc 99m Sulfur Colloid Injection is supplied in a package that contains 5 kits. All components of a kit are sterile and non-pyrogenic. Each 10mL multi-dose Reaction Vial contains, in lyophilized form, 2 mg sodium thiosulfate anhydrous, 2.3 mg edetate disodium and 18.1 mg bovine gelatin; each Solution A vial contains 1.8 mL 0.148 N hydrochloric acid solution and each Solution B vial contains 1.8 mL aqueous solution of 24.6 mg/mL sodium biphosphate anhydrous and 7.9 mg/mL sodium hydroxide. Included in each 5-kit package are one package insert and 10 radiation labels.

4 CONTRAINDICATIONS

None

5 WARNINGS AND PRECAUTIONS

5.1 Anaphylactic Reactions

Anaphylactic reactions with bronchospasm, hypotension, urticaria and rare fatalities have occurred following intravenously administered Technetium Tc 99m Sulfur Colloid Injection. Have emergency resuscitation equipment and personnel immediately available.

5.2 Radiation Risks

Radiation-emitting products, including Technetium Tc 99m Sulfur Colloid Injection, may increase the risk for cancer, especially in pediatric patients. Use the smallest dose necessary for imaging and ensure safe handling to protect the patient and health care worker. [see Dosage and Administration (2.3)].

5.3 Altered Distribution, Accumulation of Tracer in the Lungs

Technetium Tc 99m Sulfur Colloid Injection is physically unstable, and the particles will settle with time or with exposure to polyvalent cations. These larger particles are likely to be trapped by the pulmonary capillary bed following intravenous injection and result in non-uniform distribution of radioactivity. Agitate the vial adequately before administration of sulfur colloid to avoid particle aggregation and non-uniform distribution of radioactivity. Discard unused drug after 6 hours from the time of formulation. [see Dosage and Administration (2.2)]

6 ADVERSE REACTIONS

The most frequently reported adverse reactions, across all categories of use and routes of administration, include rash, allergic reaction, urticaria, anaphylaxis/anaphylactic shock, and hypotension. Less frequently reported adverse reactions are fatal cardiopulmonary arrest, seizures, dyspnea, bronchospasm, abdominal pain, flushing, nausea, vomiting, itching, fever, chills, perspiration, numbness, and dizziness. Local injection site reactions, including burning, blanching, erythema, sclerosis, swelling, eschar, and scarring, have also been reported.

7 DRUG INTERACTIONS

Specific drug-drug interactions have not been studied.

8 USE IN SPECIFIC POPULATIONS

8.1 Pregnancy

Risk Summary

Limited available data with Technetium Tc 99m Sulfur Colloid Injection use in pregnant women have not identified a drug-associated risk of major birth defects, miscarriage or adverse maternal or fetal outcomes; technetium Tc 99m crosses the placenta (see Data). Animal reproduction studies have not been conducted with Technetium Tc 99m Sulfur Colloid Injection. All radiopharmaceuticals, including Technetium Tc 99m Sulfur Colloid Injection, have a potential to cause fetal harm depending on the stage of fetal development and the magnitude of the radiopharmaceutical dose. If considering Technetium Tc 99m Sulfur Colloid Injection administration to a pregnant woman, inform the patient about the potential for adverse pregnancy outcomes based on the radiation dose from the drug and the gestational timing of exposure.

The estimated background risk of major birth defects and miscarriage for the indicated population is unknown. In the U.S. general population, the estimated background risk of major birth defects and miscarriage in clinically recognized pregnancies is 2–4% and 15–20%, respectively.

Data

Human Data

Among 14 infants born to pregnant patients exposed to Technetium Tc 99m Sulfur Colloid Injection for lymph node localization, no birth defects were reported following drug exposure.

8.2 Lactation

Risk Summary

Technetium Tc 99m is excreted in human milk during lactation. Exposure of Technetium Tc 99m Sulfur Colloid Injection to a breastfed infant can be minimized by temporary discontinuation of breastfeeding [see Clinical Considerations]. The developmental and health benefits of breastfeeding should be considered along with the mother’s clinical need for Technetium Tc 99m Sulfur Colloid Injection and any potential adverse effects on the breastfed child from Technetium Tc 99m Sulfur Colloid Injection or from the underlying maternal condition.

Clinical Considerations

To decrease radiation exposure to the breastfed infant, advise a lactating woman to pump and discard breast milk for 24 hours after administration of Technetium Tc 99m Sulfur Colloid Injection. Following higher dose procedures [greater than 370 MBq (10 mCi)], patients should minimize close contact with infants for 6 hours after receiving a Technetium Tc 99m Sulfur Colloid Injection.

8.4 Pediatric Use

The safety and efficacy of Technetium Tc 99m Sulfur Colloid kit in pediatric patients has been shown for the following indications: liver, spleen, and bone marrow imaging, and gastroesophageal and pulmonary aspiration studies.

8.5 Geriatric Use

Clinical studies of Kit for the Preparation of Technetium Tc 99m Sulfur Colloid Injection did not include sufficient numbers of subjects aged 65 and over to determine whether they respond differently from younger subjects.

10 OVERDOSAGE

The clinical consequences of overdosing with Technetium Tc 99m Sulfur Colloid Injection are not known.

11 DESCRIPTION

Kit for the Preparation of Technetium Tc 99m Sulfur Colloid Injection contains a multi-dose Reaction Vial, a Solution A vial and a Solution B vial which contain the sterile non-pyrogenic, non-radioactive ingredients necessary to produce Technetium Tc 99m Sulfur Colloid Injection for diagnostic use by subcutaneous, intraperitoneal, or intravenous injection or by oral administration.

Each 10 mL multi-dose Reaction Vial contains, in lyophilized form 2 mg sodium thiosulfate anhydrous, 2.3 mg edetate disodium and 18.1 mg bovine gelatin; a Solution A vial contains 1.8 mL of 0.148 N hydrochloric acid solution and a Solution B vial contains 1.8 mL aqueous solution of 24.6 mg/mL sodium biphosphate anhydrous and 7.9 mg/mL sodium hydroxide.

When a solution of sterile and non-pyrogenic Sodium Pertechnetate Tc 99m Injection in isotonic saline is mixed with these components, following the instructions provided with the kit, Technetium Tc 99m Sulfur Colloid Injection is formed. The product is intended for subcutaneous, intraperitoneal, or intravenous injection or for oral administration. The precise structure of Technetium Tc 99m Sulfur Colloid Injection is not known at this time.

11.1 Physical Characteristics

Technetium Tc 99m decays by isomeric transition with a physical half-life of 6.02 hours.^4The principal photon that is useful for detection and imaging studies is listed in Table 7.

Table 7. Principal Radiation Emission Data^4
Radiation | Mean Percent Per Disintegration | Mean Energy (keV)
Gamma-2 | 89.07 | 140.5

^4Kocher DC: Radioactive decay data tables. DOE/TIC-11026: 108, 1981

11.2 External Radiation

The specific gamma ray constant for Tc 99m is 0.78 R/millicurie-hr at 1cm. The first half-value layer is 0.017 cm of lead (Pb). A range of values for the relative attenuation of the radiation emitted by this radionuclide that results from interposition of various thicknesses of Pb is shown in Table 8. For example, the use of a 0.25 cm thickness of Pb will attenuate the radiation emitted by a factor of about 1,000.

Table 8. Radiation Attenuation by Lead Shielding
Shield Thickness (Pb) cm | Coefficient of Attenuation
0.017 | 0.5
0.08 | 10^-1
0.16 | 10^-2
0.25 | 10^-3
0.33 | 10^-4

To correct for physical decay of this radionuclide, the fractions that remain at selected intervals after the time of calibration are shown in Table 9.

Table 9. Physical Decay Chart: Tc 99m, half-life 6.02 hours
Hours | Fraction Remaining | Hours | Fraction Remaining
0* | 1.000 | 6 | 0.501
1 | 0.891 | 7 | 0.447
2 | 0.794 | 8 | 0.398
3 | 0.708 | 9 | 0.355
4 | 0.631 | 10 | 0.316
5 | 0.562 | 11 | 0.282
- | - | 12 | 0.251

*Calibration time

12 CLINICAL PHARMACOLOGY

12.1 Mechanism of Action

Technetium Tc 99m decays by isomeric transition, emitting a photon that can be detected for imaging purposes. [see Description (11.1)]

Following subcutaneous injection, Technetium Tc 99m Sulfur Colloid enters the lymphatic capillaries and is transported with lymph to lymph nodes. However, when there is massive nodal metastatic involvement, the normal transport to lymph nodes is lost because few normal cells remain in the node. [ see Dosage and Administration (2.4)]

Following intraperitoneal injection, Technetium Tc 99m Sulfur Colloid mixes with the peritoneal fluid; rate of clearance from the cavity allows assessment of the patency of the shunt. Clearance varies from insignificant, which may occur with complete shunt blockage, to very rapid clearance with subsequent transfer into the systemic circulation when the shunt is patent.

Following intravenous injection, Technetium Tc 99m Sulfur Colloid is taken up by the reticuloendothelial system (RES), allowing RES rich structures to be imaged.

With oral administration, Technetium Tc 99m Sulfur Colloid is not absorbed accounting for its function in esophageal transit studies, gastroesophageal reflux scintigraphy, and for the detection of pulmonary aspiration of gastric contents.

12.3 Pharmacokinetics

Following intravenous administration, Technetium Tc 99m Sulfur Colloid Injection is rapidly cleared from the blood by the reticuloendothelial system with a nominal half-life of approximately 2 1/2 minutes. Uptake of the radioactive colloid by organs of the RES is dependent upon both their relative blood flow rates and the functional capacity of the phagocytic cells. In the average patient 80 to 90% of the injected collodial particles are phagocytized by the Kupffer cells of the liver, 5 to 10% by the spleen and the balance by the bone marrow.

Following oral ingestion, Technetium Tc 99m Sulfur Colloid is distributed primarily through the gastrointestinal tract with elimination primarily through the feces.

13 NONCLINICAL TOXICOLOGY

13.1 Carcinogenesis, Mutagenesis, Impairment of Fertility

Animal studies to evaluate the carcinogenicity, mutagenesis, or reproductive toxicity potentials of Technetium Tc 99m Sulfur Colloid have not been conducted.

14 CLINICAL STUDIES

14.1 Tracer Localization to Lymph Nodes in Breast Cancer

A systematic review of 43 publications examined procedures that used the injection of Technetium Tc 99m Sulfur Colloid Injection and a blue dye (tracers) to assist surgeons in the localization of lymph nodes among patients with a primary breast cancer lesion. From these publications, 15 studies were identified for inclusion within a meta-analysis, based upon the following criteria: prospective design, minimum number of 50 lymph node localization procedures, and paired outcome data available for both Technetium Tc 99m Sulfur Colloid Injection and blue dye. Within these studies, the number of procedures ranged from 62 to 6,197; in general one procedure involved a single patient but in some uncommon situations, one patient underwent more than one procedure. The patients received subcutaneous Technetium Tc 99m Sulfur Colloid Injection doses ranging between 0.1 and 2 mCi. The mean age of patients ranged from 52 to 60 years, and almost all were female. Lymph nodes that contained radioactivity were generally localized based upon increased counts, in comparison to a background threshold (e.g., nodes containing a minimum of radioactive counts 3 times higher than background or containing at least 10 fold higher counts than contiguous nodes). Radioactivity was measured using a handheld gamma counter.

Table 10 shows the tracer localization rates where the tracer localization rate (%) is defined as the percentage of procedures which had at least one lymph node containing the specific tracer. Random effect meta-analytic measures were used for estimating various rates of tracer localization by procedure along with the respective confidence intervals. The random effect meta-analytical methods take into account the sample size of each study as well as within and between study variability. In general, most procedures involved the resection of lymph nodes in which a tracer had localized to at least one node. However, in some procedures (estimated at approximately 3.4%) neither tracer was localized to a resected lymph node. The reports were insufficient to establish the basis for failed tracer localization. [ see Dosage and Administration (2.4)]

Table 10 . Tracer Localization by Procedure – Breast Cancer*
Number of; Clinical Studies | Number of; Procedures | BD Present; (%) | SCI Present; (%) | Only BD Present; (%) | Only SCI Present; (%) | Neither; SCI nor BD Present; (%)
15 | 9,213 | 85.1 | 94.1 | 3.8 | 12.1 | 3.4
95% Confidence Intervals** |  | 81.4, 88.2 | 91.4, 96.0 | 2.8, 5.2 | 9.9, 15.0 | 2.1, 5.4

BD = blue dye, SCI = Technetium Tc 99m Sulfur Colloid Injection

* Percentage of procedures in which at least one lymph node contained the specific tracer; the percents do not add to 100% due to rounding.

** 95% Confidence Intervals are based on meta-analysis and represent the spread in the individual estimates.

In some of the publications, different methods of Technetium Tc 99m Sulfur Colloid Injection administration were compared: intradermal (ID), subareolar (SA) and intraparenchymal (IP) methods. Generally, more favorable results were seen using the ID and SA routes, with less favorable results reported when surgeons used the IP method.

14.2 Tracer Localization to Lymph Nodes in Malignant Melanoma

A systematic review of eight publications examined the use of Technetium Tc 99m Sulfur Colloid and a blue dye (tracers) to assist surgeons in the localization of lymph nodes among patients with malignant melanoma. A meta-analysis was performed using data from the studies that reported the resected lymph node content of Technetium Tc 99m Sulfur Colloid Injection and blue dye. Four of the eight publications met this criterion and were included in the meta-analysis. Within these four studies, the number of reported patients ranged from 12 to 94. The patients received subcutaneous Technetium Tc 99m Sulfur Colloid Injection doses ranging between 0.25 to 2 mCi. The patients were aged 15 to 89 years and most (53 to 70%) were male.

Lymph nodes that contained radioactivity were generally localized based upon increased counts, in comparison to a background threshold (e.g., nodes containing a minimum of radioactive counts 3 times higher than background). Radioactivity was measured using a handheld gamma counter.

Table 11 shows the tracer localization rates where the tracer localization rate (%) is defined as the percentage of patients who had at least one lymph node containing the specific tracer. Random effect meta-analytic measures were used for estimating the various rates of tracer localization by patient along with the respective confidence intervals. The random effect meta-analytical methods take into account the sample size of each study as well as within and between study variability. In general, most patients had resected lymph nodes that contained at least one of the tracers. However, in some patients (estimated at approximately 1.6%) neither tracer was localized to a resected lymph node. The reports were insufficient to establish the basis for failed tracer localization .[ see Dosage and Administration (2.4)].

Table 11 . Tracer Localization by Patient – Malignant Melanoma*
Number of; Clinical Studies | Number of; Patients | BD Present; (%) | SCI Present; (%) | Only BD Present; (%) | Only SCI Present; (%) | Neither; SCI nor BD Present; (%)
4 | 249 | 83.6 | 96.4 | 3.2 | 15.5 | 1.6
95% Confidence Intervals** |  | 73.4, 90.4 | 92.0, 98.5 | 1.4, 6.9 | 9.6, 24.1 | 0.4, 6.5

BD = blue dye, SCI = Technetium Tc 99m Sulfur Colloid Injection

* Percentage of patients in which at least one lymph node contained the specific tracer; the percents do not add to 100% due to rounding.

** 95% Confidence Intervals are based on meta-analysis and represent the spread in the individual estimates.

15 REFERENCES

- Bergqvist L, Strand S-E, Persson B, et al. Dosimetry in Lymphoscintigraphy of Tc 99m Antimony Sulfide Colloid, J Nucl Med., 23: 698-705, 1982.
- Summary of Current Radiation Dose Estimates to Humans with Various Liver Conditions from 99m Tc-Sulfur Colloid, MIRD Dose Estimate Report No 3, J Nucl Med., 16: 108A - 108B, 1975
- Henrichs et al. Estimation of age-dependent internal dose from radiopharmaceuticals, Phys. Med. Biol., 27: 775-784, 1982.
- Kocher DC: Radioactive decay data tables. DOE/TIC-11026: 108, 1981.

16 HOW SUPPLIED/STORAGE AND HANDLING

Kit for the Preparation of Technetium Tc 99m Sulfur Colloid Injection is supplied in a package that contains 5 kits. All kit components are sterile and non-pyrogenic. Each 10mL multi-dose Reaction Vial contains, in lyophilized form, 2 mg sodium thiosulfate anhydrous, 2.3 mg edetate disodium and 18.1 mg bovine gelatin; each Solution A vial contains 1.8 mL 0.148 N hydrochloric acid solution and each Solution B vial contains 1.8 mL aqueous solution of 24.6 mg/mL sodium biphosphate anhydrous and 7.9 mg/mL sodium hydroxide. Included in each 5-kit package are one package insert and 10 radiation labels.

Store the kit at 20-25°C (68-77°F) as packaged and after reconstitution.

This reagent kit for preparation of a radiopharmaceutical is approved for use by persons licensed pursuant to Section 120.547, Code of Massachusetts Regulation 105, or under equivalent license to the U.S. Nuclear Regulatory Commission or an Agreement State.

NDC #45567-0030-1

17 PATIENT COUNSELING INFORMATION

Inform patients they may experience a burning sensation at the injection site.

Inform lactating woman to pump and discard breast milk for 24 hours after administration of Technetium Tc 99m Sulfur Colloid Injection and minimize close contact with infants for 6 hours after receiving a Technetium Tc 99m Sulfur Colloid Injection (8.2).

Manufactured By:

Sun Pharmaceutical Industries, Inc.

29 Dunham Road

Billerica, MA 01821

1-800-221-7554

(for International dial: 1-781-275-7120)

PL-000001

Rev 2.0

Mar 2020

PACKAGE/LABEL PRINCIPAL DISPLAY PANEL - VIAL CONTAINER (PART 1 - 10mL multi-dose Reaction Vial)

NDC 045567-0030-1

STERILE DIAGNOSTIC MULTIDOSE NON-PYROGENIC

Multi-Dose Reaction Vial

for use in the Preparation of Technetium Tc 99m Sulfur Colloid Injection.

Each 10 mL reaction vial contains in lyophilized form 2.0 mg sodium thiosulfate anhydrous, 2.3 mg edetate disodium and 18.1 mg bovine gelatin. Usual Dosage: See complete prescribing information.

Manufactured by:

Sun Pharmaceutical Industries, Inc.

Billerica, MA 01821

PL-000004

Rev 0.3

Mar 2020

CONTAINS NO BACTERIOSTATIC PRESERVATIVE FOR
USE ONLY AFTER LABELING WITH OCIDANT-FREE
TECHENTIUM Tc 99m. Store the kit at 20-25°C

(68-77°F) [See USP] as packaged and after reconstitution with Technetium Tc 99m.

Use within 6 hours after reconstitution.

Rx ONLY

PACKAGE/LABEL - PRINCIPAL DISPLAY PANEL - VIAL CONTAINER (PART 2 - 3mL Solution A Vial)

NDC 045567-0030-1

A

Solution A vial contains 1.8mL sterile, non pyrogenic 0.148 N hydrochloric acid solution.

To be used only with the Sulfur Colloid Multi-dose Reaction Vial.

Single Use Vial-Discard Unused Portion

NOT FOR DIRECT INTRAVENOUS INJECTION.

RXONLY . STORE AT 20-25°C (68-77°F) [See USP]

Manufactured By: Sun Pharmaceutical Industries, Inc. Billerica, MA 01821

PL-000002

Rev 0.2

Mar 2020

PACKAGE/LABEL - PRINCIPAL DISPALY PANEL - VIAL CONTAINER (PART 3 - 3mL Solution B Vial)

NDC 045567-0030-1

B

Solution B vial contains 1.8mL sterile, non pyrogenic aqueous solution of 24.6 mg/mL sodium biphosphate anhydrous and 7.9 mg/mL sodium hydroxide. To be used only with the Sulfur Colloid Multi-dose Reaction Vial.

Single Use Vial-Discard Unused Portion.

NOT FOR DIRECT INTRAVENOUS INJECTION.

RXONLY . STORE AT 20-25°C (68-77°F) [See USP]

Manufactured By: Sun Pharmaceutical Industries, Inc. Billerica MA 01821

PL-000003

Rev 0.2

Mar 2020

PACKAGE/LABEL - PRINCIPAL DISPLAY PANEL - RADIATION LABEL

CAUTION RADIOACTIVE MATERIAL

STERILE, NON-PYROGENIC, DIAGNOSTIC MULTIDOSE TECHNETIUM Tc 99m SULFUR COLLOID

Subcutaneous, Intravenous, Oral, and Intraperitoneal Use

Total MBq (mCi)_____Volume_____

Assay_____MBq/mL(mCi/mL) as of _____

The 10 mL vial contents are made with 2 mg sodium thiosulfate anhydrous, 2.3 mg edetate disodium, 18.1 mg bovine gelatin, the added 1.5 mL of 0.148 N hydrochloric acid solution and the added 1.5 mL aqueous solution of 36.9 mg sodium biphosphate anhydrous and 11.9 mg sodium hydroxide. Contains no bacteriostatic preservative. For use only after labeling with oxidant-free Technetium Tc 99m. Store reconstituted vial at 20-25°C (68-77°F) [See USP]. Use within 6 hours after labeling with Technetium Tc 99m. Usual Dosage: See complete prescribing information. (SEE ENCLOSED PACKAGE INSERT) Rxonly

Manufactured by:

Sun Pharmaceutical Industries, Inc. Billerica, MA 01821

PL-000005

Rev 0.2

Mar 2020

PACKAGE/LABEL - PRINCIPAL DISPLAY PANEL - 5 VIAL BOX

NDC 045567-0030-1

Kit for the Preparation of Technetium Tc99m Sulfur Colloid Injection

CAUTION: Federal (U.S.A.) law prohibits dispensing without prescription

Rx only.

Manufactured By:

Sun Pharmaceutical Industries, Inc. Billerica, MA 01821

For Customer Service call: 1-800-221-7554

Sterile Diagnostic Multidose Non-Pyrogenic

CONTENTS: 1 package insert, 10 radiation labels, 5 multi-dose reaction vials, 5 Solution A vials and 5 Solution B vials. Each 10 mL multi-dose reaction vial contains 2 mg sodium thiosulfate anhydrous, 2.3 mg edetate disodium and 18.1 mg bovine gelatin. Each Solution A vial contains 1.8 mL 0.148 N hydrochloric acid. Each solution B vial contains 1.8 mL aqueous solution of 24.6 mg/mL sodium biphosphate anhydrous and 7.9 mg/mL sodium hydroxide. Contains no bacteriostatic preservative. For intravenous use only after labeling with oxidant-free Technetium Tc 99m.

Store the kit at 20-25°C (68-77°F) [See USP] as packaged and after reconstitution

Use within 6 hours after labeling with Technetium Tc 99m.

Usual Dosage: See complete prescribing information.

IMPORTANT: Read enclosed Package Insert for full information on preparation, use and indications.

PL-000006

Rev 0.3

Mar 2020